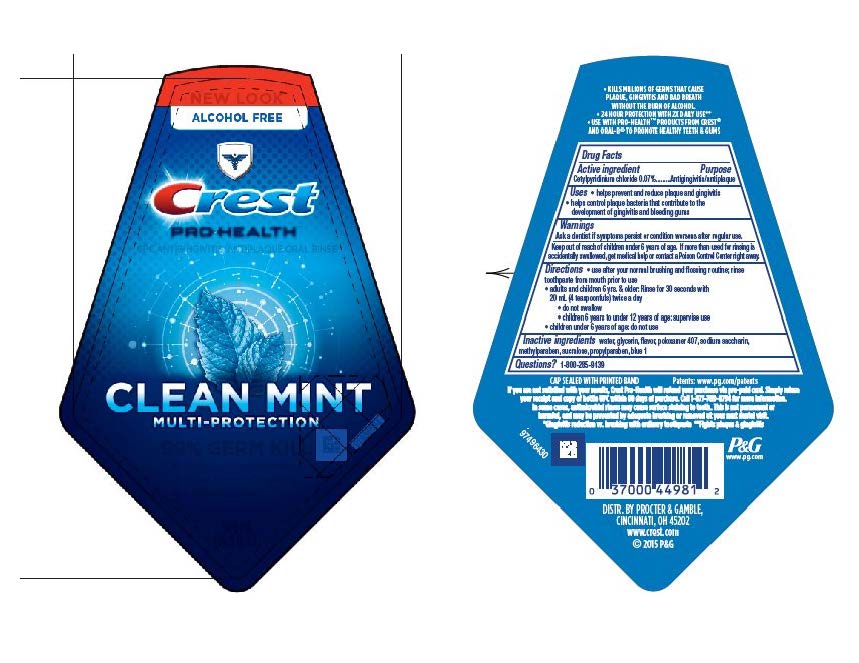 DRUG LABEL: Crest Pro-Health Multi-Protection
NDC: 37000-451 | Form: RINSE
Manufacturer: The Procter & Gamble Manufacturing Company
Category: otc | Type: HUMAN OTC DRUG LABEL
Date: 20251218

ACTIVE INGREDIENTS: CETYLPYRIDINIUM CHLORIDE 0.014 g/20 mL
INACTIVE INGREDIENTS: WATER; GLYCERIN; POLOXAMER 407; METHYLPARABEN; SACCHARIN SODIUM; PROPYLPARABEN; FD&C BLUE NO. 1

Crest® Pro-Health® Multi-Protection
Clean Mint

Drug Facts

Active ingredient

Cetylpyridinium chloride 0.07%

Purpose

Antigingivitis/Antiplaque

Uses

- helps prevent and reduce plaque and gingivitis
- helps control plaque bacteria that contribute to the development of gingivitis and bleeding gums

Warnings

ASK DOCTOR

Ask a dentist if symptoms persist or condition worsens after regular use.

Keep out of reach of children under 6 years of age. If more than used for rinsing is accidentally swallowed, get medical help or contact a Poison Control Center right away.

Directions

- use after your normal brushing and flossing routine; rinse toothpaste from mouth prior to use
- adults and children 6 yrs. & older: Rinse for 30 seconds with 20 mL (4 teaspoonfuls) twice a day
  - do not swallow
  - children 6 years to under 12 years of age: supervise use
- children under 6 years of age: do not use

Inactive ingredients

water, glycerin, flavor, poloxamer 407, methylparaben, sodium saccharin, propylparaben, blue 1

Questions?

1–800–285–9139

Dist. by Procter & Gamble,
Cincinnati OH 45202

PRINCIPAL DISPLAY PANEL - 500mL Bottle Label

ALCOHOL FREE

Crest®
PRO-HEALTH®
CPC ANTIGINGIVITIS/ANTIPLAQUE ORAL RINSE

CLEAN MINT

MULTI-PROTECTION

99% GERM KILL

- Reduces Plaque Bacteria
- HELPS PREVENT GINGIVITIS
- FRESHENS BREATH

500 mL (16.9 FL OZ)

91986694